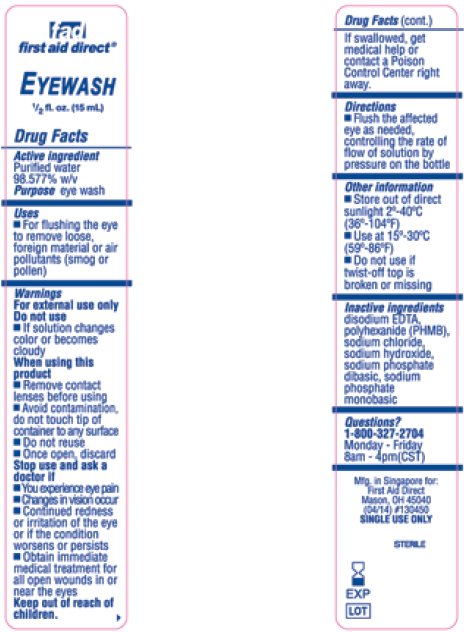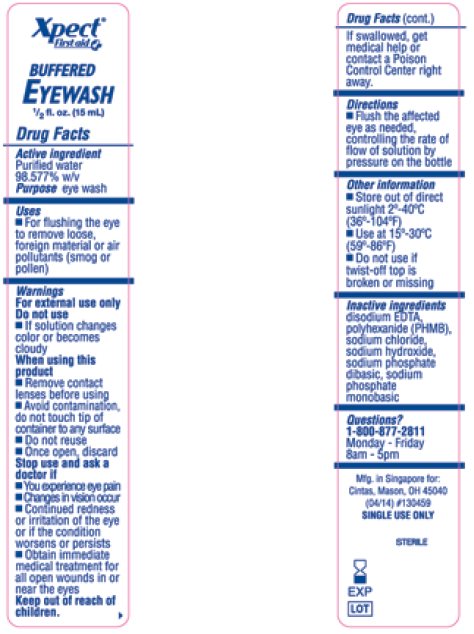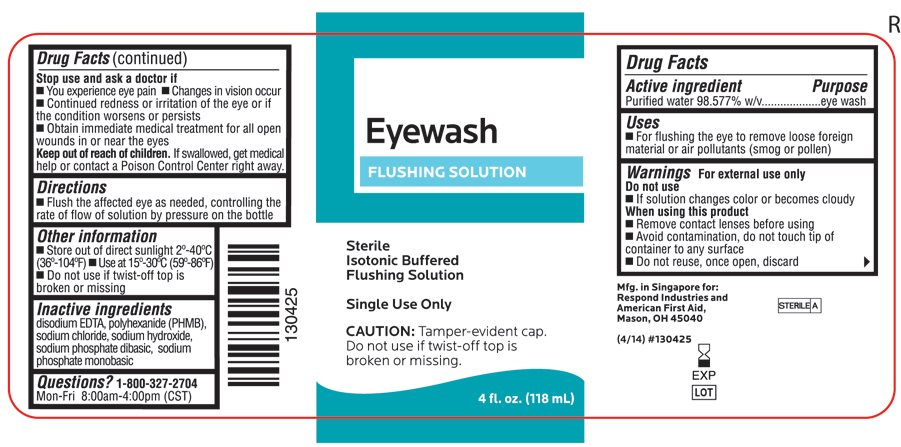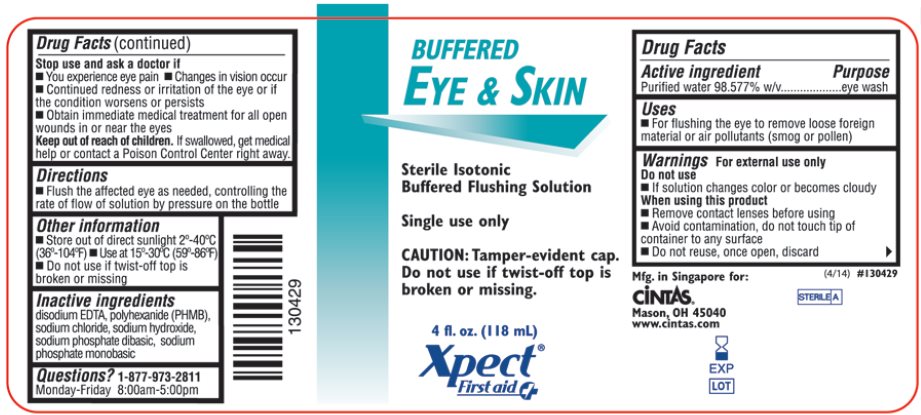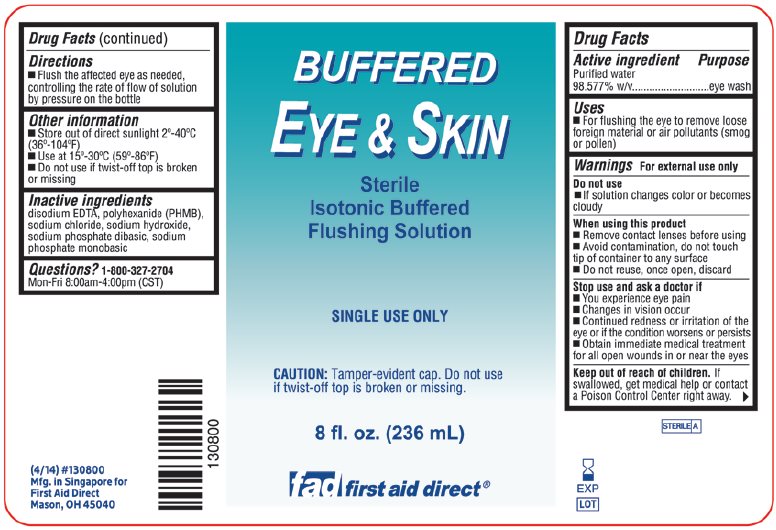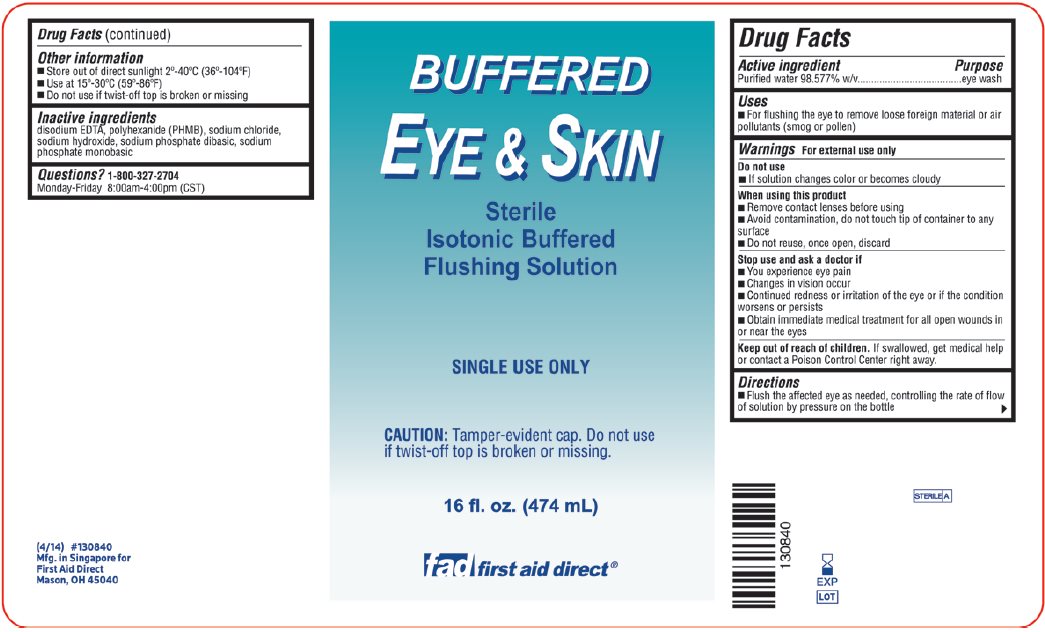 DRUG LABEL: fad first aid direct Eyewash
NDC: 42961-090 | Form: SOLUTION
Manufacturer: Cintas Corporation
Category: otc | Type: HUMAN OTC DRUG LABEL
Date: 20140715

ACTIVE INGREDIENTS: WATER 985.77 g/1000 mL
INACTIVE INGREDIENTS: POLIHEXANIDE; EDETATE DISODIUM; SODIUM HYDROXIDE; SODIUM CHLORIDE; SODIUM PHOSPHATE, DIBASIC, DODECAHYDRATE; SODIUM PHOSPHATE, MONOBASIC, DIHYDRATE

Drug Facts

Active ingredient

Purified water 98.577% w/v

Purpose

eye wash

Uses

- For flushing the eye to remove loose foreign material or air pollutants (smog or pollen)

Warnings

For external use only

Do not use

- If solution changes color or becomes cloudy

When using this product

- Remove contact lenses before using
- Avoid contamination, do not touch tip of container to any surface
- Do not reuse, once open, discard

Stop use and ask a doctor if

- You experience eye pain
- Changes in vision occur
- Continued redness or irritation of the eye or if the condition worsens or persists
- Obtain immediate medical treatment for all open wounds in or near the eyes

Keep out of reach of children. If swallowed, get medical help or contact a Poison Control Center right away.

Directions

- Flush the affected eye as needed, controlling the rate of flow of solution by pressure on the bottle

Other information

- Store out of direct sunlight 2°-40°C (36°-104°F)
- Use at 15°-30°C (59°-86°F)
- Do not use if twist-off top is broken or missing

Inactive ingredients

disodium EDTA, polyhexanide (PHMB), sodium chloride, sodium hydroxide, sodium phosphate dibasic, sodium phosphate monobasic

Package/Label Principal Display Panel – Eyewash Flushing Solution

Eyewash

FLUSHING SOLUTION

Sterile
Isotonic Buffered
Flushing Solution

Single Use Only

CAUTION: Tamper-evident cap.
Do not use if twist-off top is broken or missing.

4 fl. oz. (118 mL)

Package/Label Principal Display Panel – Xpect First aid Buffered Eye & Skin

BUFFERED
Eye & Skin

Sterile Isotonic
Buffered Flushing Solution

Single use only

CAUTION: Tamper-evident cap.
Do not use if twist-off top is broken or missing.

4 fl. oz. (118 mL)

Xpect®
First aid

Package/Label Principal Display Panel – fad first aid direct Buffered Eye & Skin

BUFFERED
Eye & Skin

Sterile
Isotonic Buffered
Flushing Solution

SINGLE USE ONLY

CAUTION: Tamper-evident cap. Do not use if twist-off top is broken or missing.

8 fl. oz. (236 mL)

fad first aid direct®

Package/Label Principal Display Panel – fad first aid direct Buffered Eye & Skin

BUFFERED
Eye & Skin

Sterile
Isotonic Buffered
Flushing Solution

SINGLE USE ONLY

CAUTION: Tamper-evident cap. Do not use if twist-off top is broken or missing.

16 fl. oz. (474 mL)

fad first aid direct®